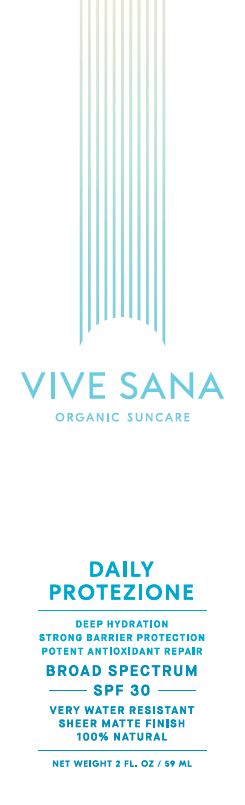 DRUG LABEL: Daily Protezione
NDC: 71556-100 | Form: LOTION
Manufacturer: Pure on Purpose, LLC
Category: otc | Type: HUMAN OTC DRUG LABEL
Date: 20190118

ACTIVE INGREDIENTS: ZINC OXIDE 17.5 g/100 g
INACTIVE INGREDIENTS: ARGAN OIL; CAMELLIA SINENSIS SEED OIL; SAFFLOWER OIL; GLYCERIN; GLYCYRRHIZA GLABRA; SUNFLOWER OIL; AVOCADO OIL; APRICOT KERNEL OIL; ROSEMARY; RASPBERRY SEED OIL; JOJOBA OIL; TOCOPHEROL

Daily Protezione Broad Spectrum SPF30 Sunscreen

Active Ingredient

Zinc Oxide (non-nano uncoated) 17.5%

Purpose

Sunscreen

USES

Helps prevent sunburn. If used as directed with other sun protection measures (see Directions), decreases the risk of skin cancer and early skin aging caused by the sun.

WARNINGS

Do not use on damaged or broken skin. When using this product keep out of eyes. Rinse with water to remove. Stop use and ask a doctor if rash occurs.

DIRECTIONS

- Apply liberally 15 minutes before sun exposure
- Children under 6 months of age—ask a doctor
- Sun Protection Measures. Spending time in the sun increases your risk of skin cancer and early skin aging. To decrease this risk, regularly use a sunscreen with a Broad Spectrum SPF value of 15 or higher & other sun protection measures including:
  - limit time in the sun, especially from 10am–2pm
  - wear long-sleeved shirts, pants, hats & sunglasses
  - reapply after 80 minutes of swimming or sweating, immediately after towel drying & at least every 2 hours

OTHER INFORMATION

Protect this product from excessive heat & direct sunlight.

INACTIVE INGREDIENTS

Argania Spinosa Kernel Oil*(Argan), Camellia Sinensis (Green Tea) Seed Oil*, Carthamus Tinctorius (Safflower) Seed Oil*, Cera Alba (Beeswax)*, Glycerin*, Glycyrrhiza Glabra (Licorice) Root Extract, Helianthus Annuus (Sunflower) Seed Oil*, Iron Oxides (CI 77491), (CI 77492) and (CI 77499), Jojoba Esters, Persea Gratissima (Avocado) Oil*, Prunus Armeniaca (Apricot) Kernel Oil*, Rosmarinus Officinalis (Rosemary) Leaf Extract, Rubus Idaeus (Raspberry) Seed Oil, Simmondsia Chinensis (Jojoba) Seed Oil*, Tocopherol (Vitamin E). *denotes certified organic

Package/Label Principal Display Panel

VIVE SANA
ORGANIC SUNCARE

DAILY
PROTEZIONE
DEEP HYDRATION
STRONG BARRIER PROTECTION
POTENT ANTIOXIDANT REPAIR
BROAD SPECTRUM
-SPF 30-
VERY WATER RESISTANT
SHEER MATTE FINISH
100% NATURAL

NET WEIGHT 2 FL. OZ / 59 ML

Label